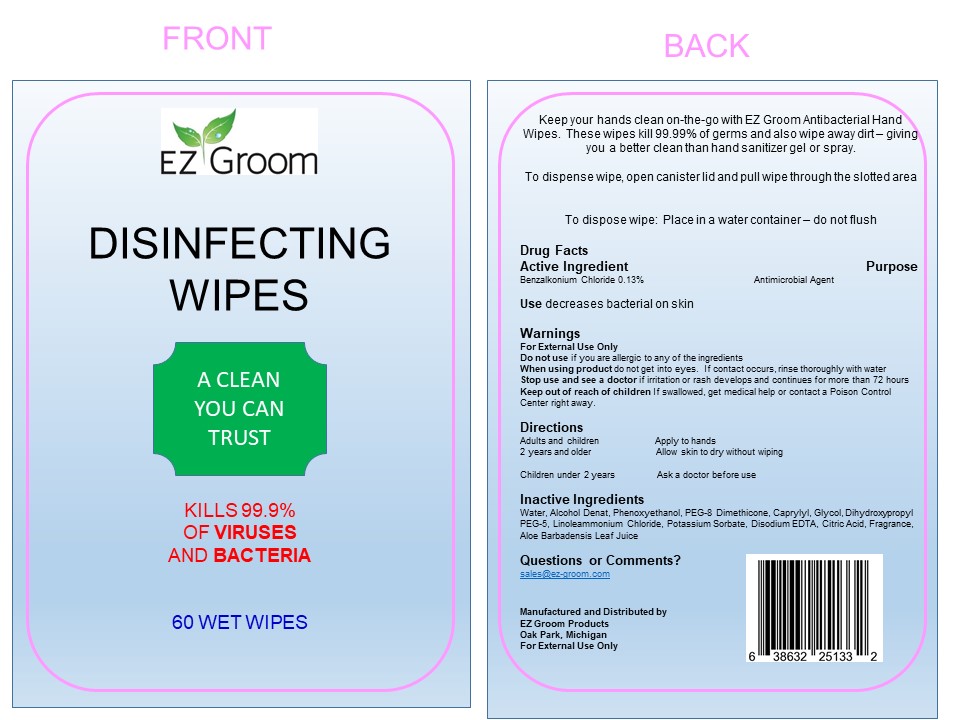 DRUG LABEL: EZ Groom Hand Sanitizing Wipes
NDC: 77032-0003 | Form: CLOTH
Manufacturer: EZ-Groom
Category: otc | Type: HUMAN OTC DRUG LABEL
Date: 20220114

ACTIVE INGREDIENTS: BENZALKONIUM CHLORIDE 0.13 g/100 mL
INACTIVE INGREDIENTS: WATER 98 g/100 mL

Active Ingredient Purpose

Benzalkonium Chloride 0.13% Purpose Antimicrobial Agent

Purpose

Antibacterial Hand Wipes

Indications and Use

Hand sanitizing wipes to help reduce bacterial that can potentially cause disease. For use when soap and water are not available.

Warnings

For external use only.

Do not use if you are allergic to any of the ingredients

When using product do not get into eyes. If contact occurs, rinse thoroughly with water

Stop use and see a doctor if irritation or rash develops and continues for more than 72 hours

Keep out of reach of children If swallowed, get medical help or contact a Poison Control Center right away.

Inactive Ingredients

Water, Alcohol Denat, Phenoxyethanol, PEG-8 Dimethicone, Caprylyl, Glycol, Dihydroxypropyl PEG-5, Linoleammonium Chloride, Potassium Sorbate, Disodium EDTA, Citric Acid, Fragrance, Aloe Barbadensis Leaf Juice

Questions or Comments?

sales@ez-groom.com

Manufactured and Distributed by

EZ Groom Products

Oak Park, Michigan

Dosage

Use towel to thoroughly moisten hands. Discard towel in a waste container.